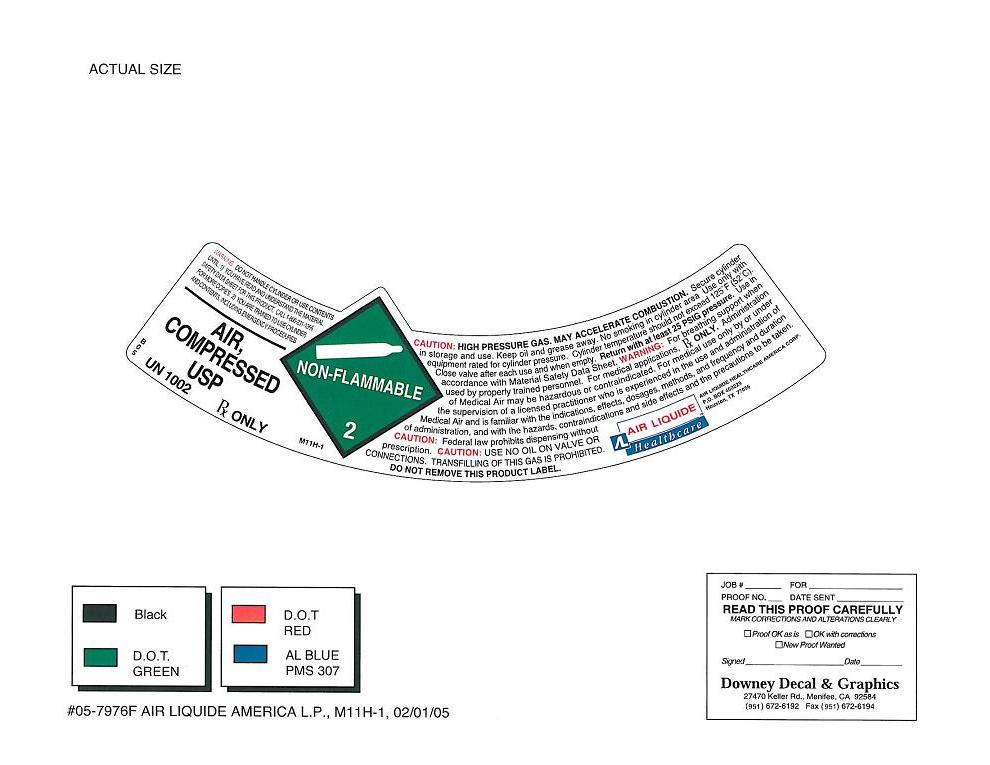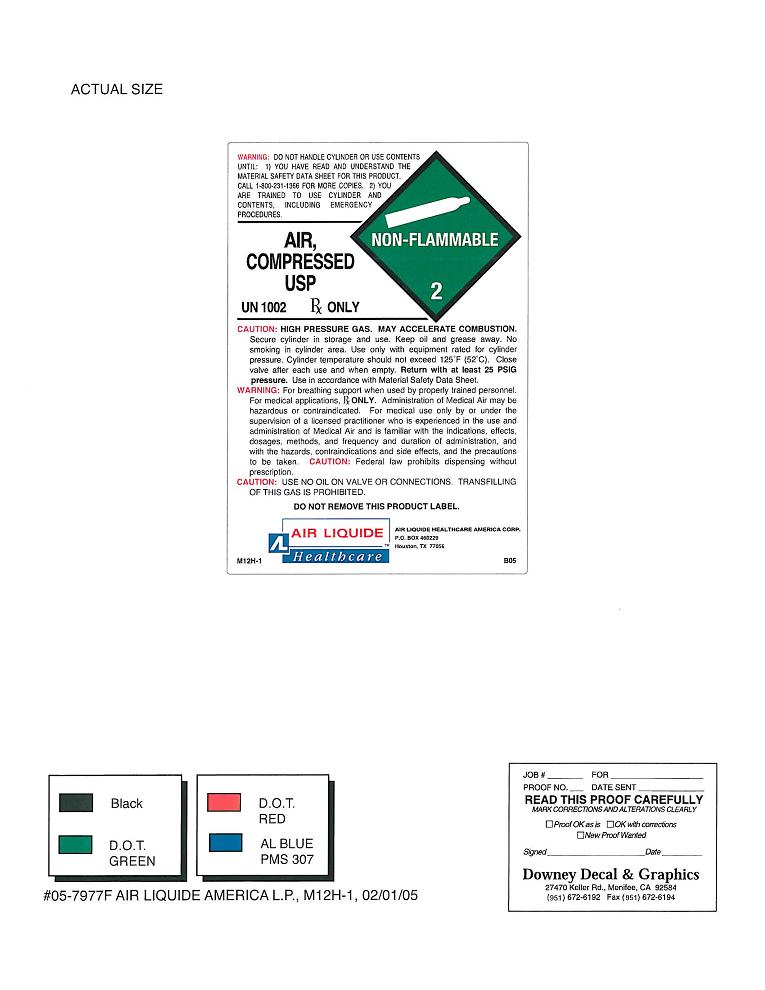 DRUG LABEL: Air
NDC: 64735-080 | Form: GAS
Manufacturer: Air Liquide Healthcare America Corporation
Category: prescription | Type: HUMAN PRESCRIPTION DRUG LABEL
Date: 20100625

ACTIVE INGREDIENTS: Oxygen 23 L/100 L; Nitrogen 77 L/100 L

AIR USP COMPRESSED

Cylinders B, E, 22, 27, 44, 49

Enter section text here

WARNINGS

Enter section text here

WARNING: DO NOT HANDLE CYLINDER OR USE CONTENTS UNTIL: 1) YOU HAVE READ AND UNDERSTAND THE MATERIAL SAFETY DATA SHEET FOR THIS PRODUCT. CALL 1-800-231-1366 FOR MORE COPIES. 2) YOU ARE TRAINED TO USE CYLINDER AND CONTENTS, INCLUDING EMERGENCY PROCEDURES.
CAUTION: HIGH PRESSURE GAS. MAY ACCELERATE COMBUSTION. Secure cylinder in storage and use. Keep oil and grease away. No smoking in cylinder area. Use only with equipment rated for cylinder pressure. Cylinder temperatures should not exceed 125°F (52°C). Close valve after each use and when empty. Return with at least 25 PSIG pressure. Use in accordance with Material Safety Data Sheet.
WARNING: For breathing support when used by properly trained personnel. For medical applications, Rx ONLY. Administration of Medical Air may be hazardous or contraindicated. For medical use only by or under the supervision of a licensed practitioner who is experienced in the use and administration of Medical Air and is familiar with the indications, effects, dosages, methods, and frequency and duration of administration, and with the hazards, contraindications and side effects and the precautions to be taken.
CAUTION: Federal law prohibits dispensing without prescription.
CAUTION: USE NO OIL ON VALVE OR CONNECTIONS. TRANSFILLING OF THIS GAS IS PROHIBITED.
DO NOT REMOVE THIS PRODUCT LABEL.